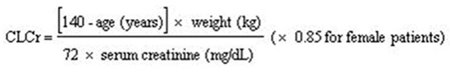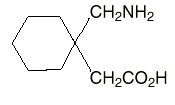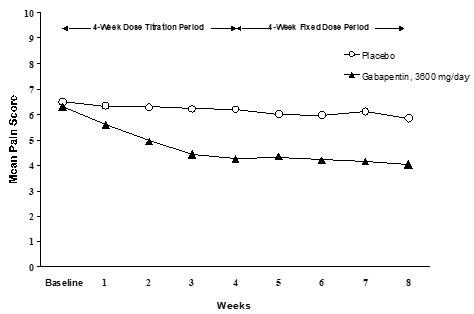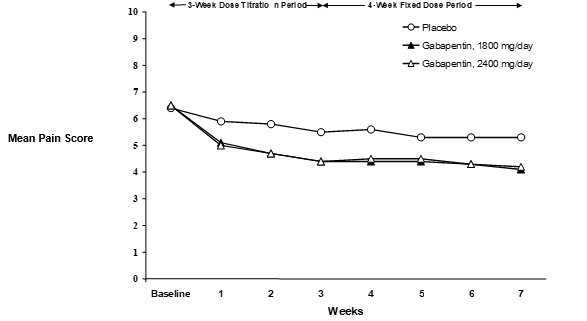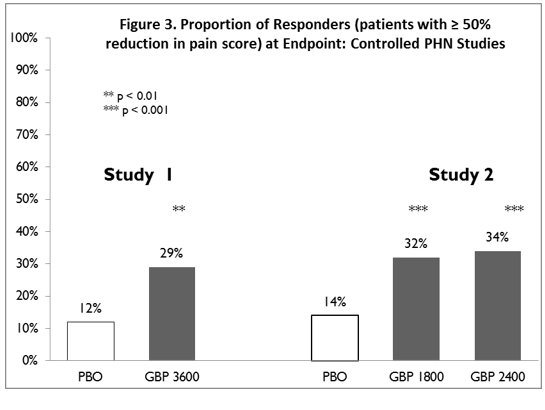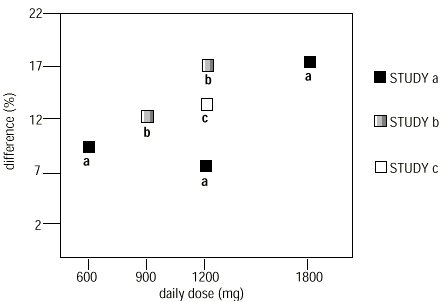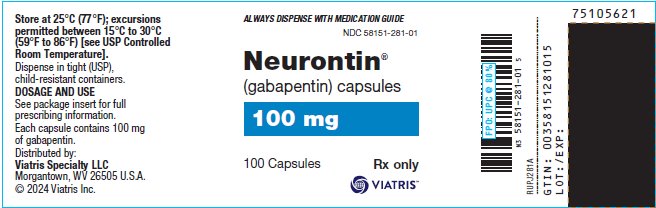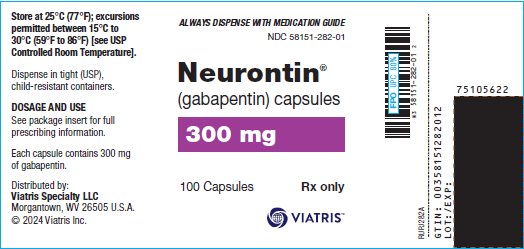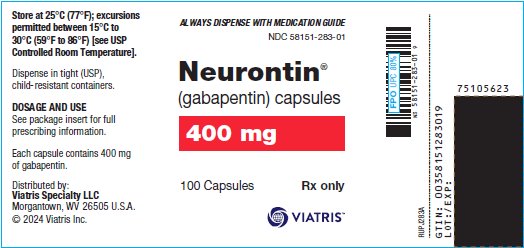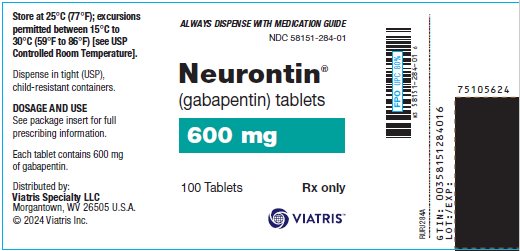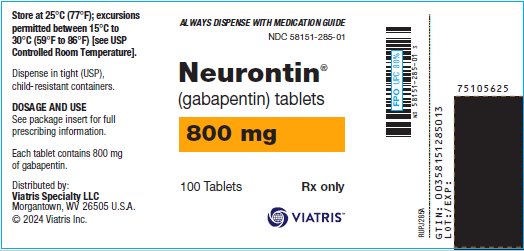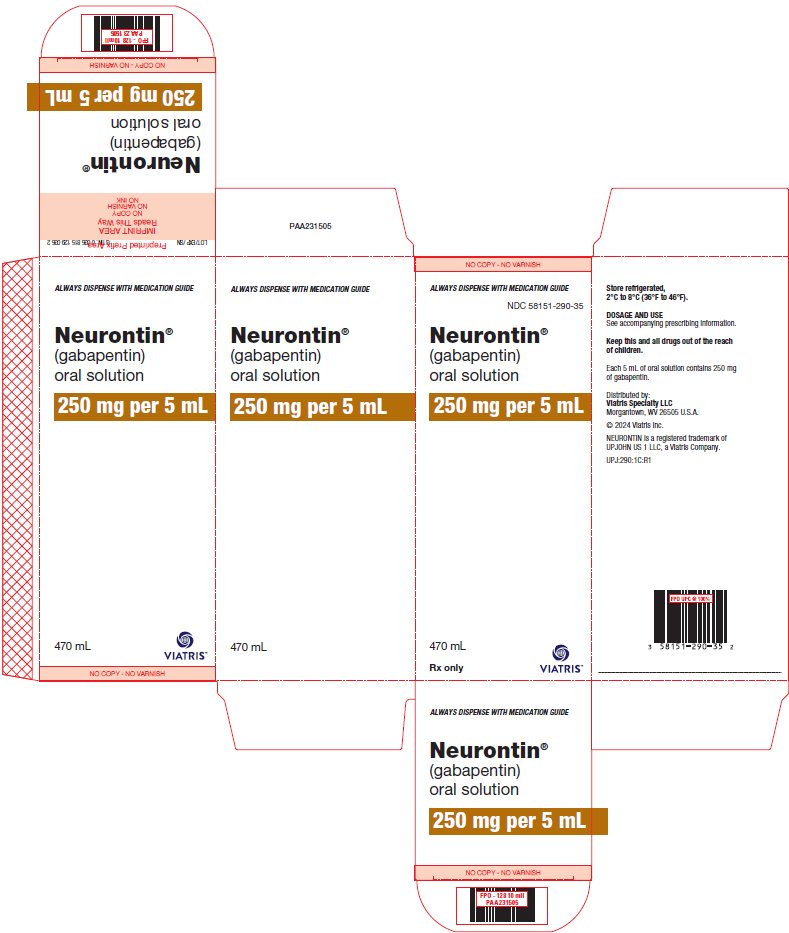 DRUG LABEL: Neurontin
NDC: 58151-281 | Form: CAPSULE
Manufacturer: Viatris Specialty LLC
Category: prescription | Type: HUMAN PRESCRIPTION DRUG LABEL
Date: 20250415

ACTIVE INGREDIENTS: GABAPENTIN 100 mg/1 1
INACTIVE INGREDIENTS: LACTOSE, UNSPECIFIED FORM; STARCH, CORN; TALC; GELATIN, UNSPECIFIED; TITANIUM DIOXIDE; FD&C BLUE NO. 2

HIGHLIGHTS OF PRESCRIBING INFORMATION

These highlights do not include all the information needed to use NEURONTIN safely and effectively. See full prescribing information for NEURONTIN.
NEURONTIN® (gabapentin) capsules, for oral use
NEURONTIN® (gabapentin) tablets, for oral use
NEURONTIN® (gabapentin) oral solution
Initial U.S. Approval: 1993

RECENT MAJOR CHANGES

Warnings and Precautions (5.5, 5.6) 4/2025

Warnings and Precautions, removal-
Sudden and Unexplained Death in Patients with Epilepsy (5.10) 4/2025

1 INDICATIONS AND USAGE

NEURONTIN is indicated for:

- Postherpetic neuralgia in adults (1)
- Adjunctive therapy in the treatment of partial onset seizures, with and without secondary generalization, in adults and pediatric patients 3 years and older with epilepsy (1)

2 DOSAGE AND ADMINISTRATION

- Postherpetic Neuralgia (2.1)
  - Dose can be titrated up as needed to a dose of 1800 mg/day
  - Day 1: Single 300 mg dose
  - Day 2: 600 mg/day (i.e., 300 mg two times a day)
  - Day 3: 900 mg/day (i.e., 300 mg three times a day)
- Epilepsy with Partial Onset Seizures (2.2)
  - Patients 12 years of age and older: starting dose is 300 mg three times daily; may be titrated up to 600 mg three times daily
  - Patients 3 to 11 years of age: starting dose range is 10 to 15 mg/kg/day, given in three divided doses; recommended dose in patients 3 to 4 years of age is 40 mg/kg/day, given in three divided doses; the recommended dose in patients 5 to 11 years of age is 25 to 35 mg/kg/day, given in three divided doses. The recommended dose is reached by upward titration over a period of approximately 3 days
- Dose should be adjusted in patients with reduced renal function (2.3, 2.4)

3 DOSAGE FORMS AND STRENGTHS

- Capsules: 100 mg, 300 mg, and 400 mg (3)
- Tablets: 600 mg, and 800 mg (3)
- Oral Solution: 250 mg/5mL (3)

4 CONTRAINDICATIONS

Known hypersensitivity to gabapentin or its ingredients (4)

5 WARNINGS AND PRECAUTIONS

- Drug Reaction with Eosinophilia and Systemic Symptoms (Multiorgan hypersensitivity): Discontinue if alternative etiology is not established (5.1)
- Anaphylaxis and Angioedema: Discontinue and evaluate patient immediately (5.2)
- Driving Impairment; Somnolence/Sedation and Dizziness: Warn patients not to drive until they have gained sufficient experience to assess whether their ability to drive or operate heavy machinery will be impaired (5.3, 5.4)
- Suicidal Behavior and Ideation: Monitor for suicidal thoughts/behavior (5.5)
- Abrupt or rapid discontinuation may increase the risk for seizures. Withdrawal symptoms, or suicidal behavior and ideation have been observed after discontinuation (5.6)
- Respiratory Depression: May occur with NEURONTIN when used with concomitant central nervous system (CNS) depressants, including opioids, or in the setting of underlying respiratory impairment. Monitor patients and adjust dosage as appropriate (5.8)
- Neuropsychiatric Adverse Reactions in Children 3 to 12 Years of Age: Monitor for such events (5.9)

6 ADVERSE REACTIONS

Most common adverse reactions (incidence ≥8% and at least twice that for placebo) were:

- Postherpetic neuralgia: Dizziness, somnolence, and peripheral edema (6.1)
- Epilepsy in patients >12 years of age: Somnolence, dizziness, ataxia, fatigue, and nystagmus (6.1)
- Epilepsy in patients 3 to 12 years of age: Viral infection, fever, nausea and/or vomiting, somnolence, and hostility (6.1)

To report SUSPECTED ADVERSE REACTIONS, contact Viatris at 1-877-446-3679 (1-877-4-INFO-RX) or FDA at 1-800-FDA-1088 or www.fda.gov/medwatch.

7 DRUG INTERACTIONS

Concentrations increased by morphine; may need dose adjustment (5.4, 7.1)

8 USE IN SPECIFIC POPULATIONS

Pregnancy: Based on animal data, may cause fetal harm (8.1)

FULL PRESCRIBING INFORMATION

1 INDICATIONS AND USAGE

NEURONTIN® is indicated for:

- Management of postherpetic neuralgia in adults
- Adjunctive therapy in the treatment of partial onset seizures, with and without secondary generalization, in adults and pediatric patients 3 years and older with epilepsy

2 DOSAGE AND ADMINISTRATION

2.1 Dosage for Postherpetic Neuralgia

In adults with postherpetic neuralgia, NEURONTIN may be initiated on Day 1 as a single 300 mg dose, on Day 2 as 600 mg/day (300 mg two times a day), and on Day 3 as 900 mg/day (300 mg three times a day). The dose can subsequently be titrated up as needed for pain relief to a dose of 1800 mg/day (600 mg three times a day). In clinical studies, efficacy was demonstrated over a range of doses from 1800 mg/day to 3600 mg/day with comparable effects across the dose range; however, in these clinical studies, the additional benefit of using doses greater than 1800 mg/day was not demonstrated.

2.2 Dosage for Epilepsy with Partial Onset Seizures

Patients 12 Years of Age and Above

The starting dose is 300 mg three times a day. The recommended maintenance dose of NEURONTIN is 300 mg to 600 mg three times a day. Dosages up to 2400 mg/day have been administered in long-term clinical studies. Doses of 3600 mg/day have also been administered to a small number of patients for a relatively short duration. Administer NEURONTIN three times a day using 300 mg or 400 mg capsules, or 600 mg or 800 mg tablets. The maximum time between doses should not exceed 12 hours.

Pediatric Patients Age 3 to 11 Years

The starting dose range is 10 mg/kg/day to 15 mg/kg/day, given in three divided doses, and the recommended maintenance dose reached by upward titration over a period of approximately 3 days. The recommended maintenance dose of NEURONTIN in patients 3 to 4 years of age is 40 mg/kg/day, given in three divided doses. The recommended maintenance dose of NEURONTIN in patients 5 to 11 years of age is 25 mg/kg/day to 35 mg/kg/day, given in three divided doses. NEURONTIN may be administered as the oral solution, capsule, or tablet, or using combinations of these formulations. Dosages up to 50 mg/kg/day have been administered in a long-term clinical study. The maximum time interval between doses should not exceed 12 hours.

2.3 Dosage Adjustment in Patients with Renal Impairment

Dosage adjustment in patients 12 years of age and older with renal impairment or undergoing hemodialysis is recommended, as follows (see dosing recommendations above for effective doses in each indication):

TABLE 1. NEURONTIN Dosage Based on Renal Function
Renal Function Creatinine Clearance (mL/min) | Total Daily Dose Range; (mg/day) | Dose Regimen; (mg)
≥ 60 | 900 to 3600 | 300 TID | 400 TID | 600 TID | 800 TID | 1200 TID
>30 to 59 | 400 to 1400 | 200 BID | 300 BID | 400 BID | 500 BID | 700 BID
>15 to 29 | 200 to 700 | 200 QD | 300 QD | 400 QD | 500 QD | 700 QD
15 [For patients with creatinine clearance <15 mL/min, reduce daily dose in proportion to creatinine clearance (e.g., patients with a creatinine clearance of 7.5 mL/min should receive one-half the daily dose that patients with a creatinine clearance of 15 mL/min receive).] | 100 to 300 | 100 QD | 125 QD | 150 QD | 200 QD | 300 QD
 |  | Post-Hemodialysis Supplemental Dose (mg) [Patients on hemodialysis should receive maintenance doses based on estimates of creatinine clearance as indicated in the upper portion of the table and a supplemental post-hemodialysis dose administered after each 4 hours of hemodialysis as indicated in the lower portion of the table.]
Hemodialysis |  | 125 | 150 | 200 | 250 |  | 350
TID = Three times a day; BID = Two times a day; QD = Single daily dose

Creatinine clearance (CLCr) is difficult to measure in outpatients. In patients with stable renal function, creatinine clearance can be reasonably well estimated using the equation of Cockcroft and Gault:

The use of NEURONTIN in patients less than 12 years of age with compromised renal function has not been studied.

2.4 Dosage in Elderly

Because elderly patients are more likely to have decreased renal function, care should be taken in dose selection, and dose should be adjusted based on creatinine clearance values in these patients.

2.5 Administration Information

Administer NEURONTIN orally with or without food.

NEURONTIN capsules should be swallowed whole with water.

Inform patients that, should they divide the scored 600 mg or 800 mg NEURONTIN tablet in order to administer a half-tablet, they should take the unused half-tablet as the next dose. Half-tablets not used within 28 days of dividing the scored tablet should be discarded.

If the NEURONTIN dose is reduced, discontinued, or substituted with an alternative medication, this should be done gradually over a minimum of 1 week (a longer period may be needed at the discretion of the prescriber).

3 DOSAGE FORMS AND STRENGTHS

Capsules

- 100 mg: white hard gelatin capsules printed with “VLE” on the body and “Neurontin/100 mg” on the cap
- 300 mg: yellow hard gelatin capsules printed with “VLE” on the body and “Neurontin/300 mg” on the cap
- 400 mg: orange hard gelatin capsules printed with “VLE” on the body and “Neurontin/400 mg” on the cap

Tablets

- 600 mg: white elliptical film-coated scored tablets debossed with “NT” and “16” on one side
- 800 mg: white elliptical film-coated scored tablets debossed with “NT” and “26” on one side

Oral solution

- 250 mg per 5 mL (50 mg per mL), clear colorless to slightly yellow solution

4 CONTRAINDICATIONS

NEURONTIN is contraindicated in patients who have demonstrated hypersensitivity to the drug or its ingredients.

5 WARNINGS AND PRECAUTIONS

5.1 Drug Reaction with Eosinophilia and Systemic Symptoms (DRESS)/Multiorgan Hypersensitivity

Drug Reaction with Eosinophilia and Systemic Symptoms (DRESS), also known as multiorgan hypersensitivity, has occurred with NEURONTIN. Some of these reactions have been fatal or life-threatening. DRESS typically, although not exclusively, presents with fever, rash, and/or lymphadenopathy, in association with other organ system involvement, such as hepatitis, nephritis, hematological abnormalities, myocarditis, or myositis sometimes resembling an acute viral infection. Eosinophilia is often present. This disorder is variable in its expression, and other organ systems not noted here may be involved.

It is important to note that early manifestations of hypersensitivity, such as fever or lymphadenopathy, may be present even though rash is not evident. If such signs or symptoms are present, the patient should be evaluated immediately. NEURONTIN should be discontinued if an alternative etiology for the signs or symptoms cannot be established.

5.2 Anaphylaxis and Angioedema

NEURONTIN can cause anaphylaxis and angioedema after the first dose or at any time during treatment. Signs and symptoms in reported cases have included difficulty breathing, swelling of the lips, throat, and tongue, and hypotension requiring emergency treatment. Patients should be instructed to discontinue NEURONTIN and seek immediate medical care should they experience signs or symptoms of anaphylaxis or angioedema.

5.3 Effects on Driving and Operating Heavy Machinery

Patients taking NEURONTIN should not drive until they have gained sufficient experience to assess whether NEURONTIN impairs their ability to drive. Driving performance studies conducted with a prodrug of gabapentin (gabapentin enacarbil tablet, extended-release) indicate that gabapentin may cause significant driving impairment. Prescribers and patients should be aware that patients’ ability to assess their own driving competence, as well as their ability to assess the degree of somnolence caused by NEURONTIN, can be imperfect. The duration of driving impairment after starting therapy with NEURONTIN is unknown. Whether the impairment is related to somnolence [see Warnings and Precautions (5.4)] or other effects of NEURONTIN is unknown.

Moreover, because NEURONTIN causes somnolence and dizziness [see Warnings and Precautions (5.4)], patients should be advised not to operate complex machinery until they have gained sufficient experience on NEURONTIN to assess whether NEURONTIN impairs their ability to perform such tasks.

5.4 Somnolence/Sedation and Dizziness

During the controlled epilepsy trials in patients older than 12 years of age receiving doses of NEURONTIN up to 1800 mg daily, somnolence, dizziness, and ataxia were reported at a greater rate in patients receiving NEURONTIN compared to placebo: i.e., 19% in drug versus 9% in placebo for somnolence, 17% in drug versus 7% in placebo for dizziness, and 13% in drug versus 6% in placebo for ataxia. In these trials somnolence, ataxia and fatigue were common adverse reactions leading to discontinuation of NEURONTIN in patients older than 12 years of age, with 1.2%, 0.8% and 0.6% discontinuing for these events, respectively.

During the controlled trials in patients with post-herpetic neuralgia, somnolence, and dizziness were reported at a greater rate compared to placebo in patients receiving NEURONTIN, in dosages up to 3600 mg per day: i.e., 21% in NEURONTIN-treated patients versus 5% in placebo-treated patients for somnolence and 28% in NEURONTIN-treated patients versus 8% in placebo-treated patients for dizziness. Dizziness and somnolence were among the most common adverse reactions leading to discontinuation of NEURONTIN.

Patients should be carefully observed for signs of central nervous system (CNS) depression, such as somnolence and sedation, when NEURONTIN is used with other drugs with sedative properties because of potential synergy. In addition, patients who require concomitant treatment with morphine may experience increases in gabapentin concentrations and may require dose adjustment [see Drug Interactions (7.1)].

5.5 Suicidal Behavior and Ideation

Antiepileptic drugs (AEDs), including NEURONTIN, increase the risk of suicidal thoughts or behavior in patients taking these drugs for any indication. Suicidal behavior and ideation have also been reported in patients after discontinuation of NEURONTIN [see Warnings and Precautions (5.6)]. Patients treated with any AED for any indication should be monitored for the emergence or worsening of depression, suicidal thoughts or behavior, and/or any unusual changes in mood or behavior.

Pooled analyses of 199 placebo-controlled clinical trials (mono- and adjunctive therapy) of 11 different AEDs showed that patients randomized to one of the AEDs had approximately twice the risk (adjusted Relative Risk 1.8, 95% CI:1.2, 2.7) of suicidal thinking or behavior compared to patients randomized to placebo. In these trials, which had a median treatment duration of 12 weeks, the estimated incidence rate of suicidal behavior or ideation among 27,863 AED-treated patients was 0.43%, compared to 0.24% among 16,029 placebo-treated patients, representing an increase of approximately one case of suicidal thinking or behavior for every 530 patients treated. There were four suicides in drug-treated patients in the trials and none in placebo-treated patients, but the number is too small to allow any conclusion about drug effect on suicide.

The increased risk of suicidal thoughts or behavior with AEDs was observed as early as one week after starting drug treatment with AEDs and persisted for the duration of treatment assessed. Because most trials included in the analysis did not extend beyond 24 weeks, the risk of suicidal thoughts or behavior beyond 24 weeks could not be assessed.

The risk of suicidal thoughts or behavior was generally consistent among drugs in the data analyzed. The finding of increased risk with AEDs of varying mechanisms of action and across a range of indications suggests that the risk applies to all AEDs used for any indication. The risk did not vary substantially by age (5-100 years) in the clinical trials analyzed. Table 2 shows absolute and relative risk by indication for all evaluated AEDs.

TABLE 2. Risk by Indication for Antiepileptic Drugs in the Pooled Analysis
Indication | Placebo Patients with Events Per 1,000 Patients | Drug Patients with Events Per 1,000 Patients | Relative Risk: Incidence of Events in Drug Patients/Incidence in Placebo Patients | Risk Difference: Additional Drug Patients with Events Per 1,000 Patients
Epilepsy | 1.0 | 3.4 | 3.5 | 2.4
Psychiatric | 5.7 | 8.5 | 1.5 | 2.9
Other | 1.0 | 1.8 | 1.9 | 0.9
Total | 2.4 | 4.3 | 1.8 | 1.9

The relative risk for suicidal thoughts or behavior was higher in clinical trials for epilepsy than in clinical trials for psychiatric or other conditions, but the absolute risk differences were similar for the epilepsy and psychiatric indications.

Anyone considering prescribing NEURONTIN or any other AED must balance the risk of suicidal thoughts or behavior with the risk of untreated illness. Epilepsy and many other illnesses for which AEDs are prescribed are themselves associated with morbidity and mortality and an increased risk of suicidal thoughts and behavior. Should suicidal thoughts and behavior emerge during treatment, the prescriber needs to consider whether the emergence of these symptoms in any given patient may be related to the illness being treated.

Patients, their caregivers, and families should be informed that AEDs increase the risk of suicidal thoughts and behavior and should be advised of the need to be alert for the emergence or worsening of the signs and symptoms of depression, any unusual changes in mood or behavior, or the emergence of suicidal thoughts, behavior, or thoughts about self-harm. Behaviors of concern should be reported immediately to healthcare providers.

5.6 Increased Risk of Seizures and Other Adverse Reactions with Abrupt or Rapid Discontinuation

Antiepileptic drugs should not be abruptly discontinued because of the possibility of increasing seizure frequency.

When NEURONTIN is being discontinued, the dose should be tapered over at least a one-week period.

After discontinuation of short-term and long-term treatment with gabapentin, withdrawal symptoms have been observed in some patients [see Adverse Reactions (6.2) and Drug Abuse and Dependence (9.3)]. Suicidal behavior and ideation have also been reported in patients after discontinuation of NEURONTIN [see Warnings and Precautions (5.5)].

5.7 Status Epilepticus

In the placebo-controlled epilepsy studies in patients >12 years of age, the incidence of status epilepticus in patients receiving NEURONTIN was 0.6% (3 of 543) versus 0.5% in patients receiving placebo (2 of 378). Among the 2074 patients >12 years of age treated with NEURONTIN across all epilepsy studies (controlled and uncontrolled), 31 (1.5%) had status epilepticus. Of these, 14 patients had no prior history of status epilepticus either before treatment or while on other medications. Because adequate historical data are not available, it is impossible to say whether or not treatment with NEURONTIN is associated with a higher or lower rate of status epilepticus than would be expected to occur in a similar population not treated with NEURONTIN.

5.8 Respiratory Depression

There is evidence from case reports, human studies, and animal studies associating gabapentin with serious, life-threatening, or fatal respiratory depression when coadministered with CNS depressants, including opioids, or in the setting of underlying respiratory impairment. When the decision is made to co-prescribe NEURONTIN with another CNS depressant, particularly an opioid, or to prescribe NEURONTIN to patients with underlying respiratory impairment, monitor patients for symptoms of respiratory depression and sedation, and consider initiating NEURONTIN at a low dose. The management of respiratory depression may include close observation, supportive measures, and reduction or withdrawal of CNS depressants (including NEURONTIN).

5.9 Neuropsychiatric Adverse Reactions (Pediatric Patients 3 to 12 Years of Age)

Gabapentin use in pediatric patients with epilepsy 3 to 12 years of age is associated with the occurrence of CNS related adverse reactions. The most significant of these can be classified into the following categories: 1) emotional lability (primarily behavioral problems), 2) hostility, including aggressive behaviors, 3) thought disorder, including concentration problems and change in school performance, and 4) hyperkinesia (primarily restlessness and hyperactivity). Among the gabapentin-treated patients, most of the reactions were mild to moderate in intensity.

In controlled clinical epilepsy trials in pediatric patients 3 to 12 years of age, the incidence of these adverse reactions was: emotional lability 6% (gabapentin-treated patients) versus 1.3% (placebo-treated patients); hostility 5.2% versus 1.3%; hyperkinesia 4.7% versus 2.9%; and thought disorder 1.7% versus 0%. One of these reactions, a report of hostility, was considered serious. Discontinuation of gabapentin treatment occurred in 1.3% of patients reporting emotional lability and hyperkinesia and 0.9% of gabapentin-treated patients reporting hostility and thought disorder. One placebo-treated patient (0.4%) withdrew due to emotional lability.

5.10 Tumorigenic Potential

In an oral carcinogenicity study, gabapentin increased the incidence of pancreatic acinar cell tumors in rats [see Nonclinical Toxicology (13.1)]. The clinical significance of this finding is unknown. Clinical experience during gabapentin’s premarketing development provides no direct means to assess its potential for inducing tumors in humans.

In clinical studies in adjunctive therapy in epilepsy comprising 2,085 patient-years of exposure in patients >12 years of age, new tumors were reported in 10 patients (2 breast, 3 brain, 2 lung, 1 adrenal, 1 non-Hodgkin’s lymphoma, 1 endometrial carcinoma in situ), and preexisting tumors worsened in 11 patients (9 brain, 1 breast, 1 prostate) during or up to 2 years following discontinuation of NEURONTIN. Without knowledge of the background incidence and recurrence in a similar population not treated with NEURONTIN, it is impossible to know whether the incidence seen in this cohort is or is not affected by treatment.

6 ADVERSE REACTIONS

The following serious adverse reactions are discussed in greater detail in other sections:

- Drug Reaction with Eosinophilia and Systemic Symptoms (DRESS)/Multiorgan Hypersensitivity [see Warnings and Precautions (5.1)]
- Anaphylaxis and Angioedema [see Warnings and Precautions (5.2)]
- Somnolence/Sedation and Dizziness [see Warnings and Precautions (5.4)]
- Suicidal Behavior and Ideation [see Warnings and Precautions (5.5)]
- Increased Risk of Seizures and Other Adverse Reactions with Abrupt or Rapid Discontinuation [see Warnings and Precautions (5.6)]
- Status Epilepticus [see Warnings and Precautions (5.7)]
- Respiratory Depression [see Warnings and Precautions (5.8)]
- Neuropsychiatric Adverse Reactions (Pediatric Patients 3 to 12 Years of Age) [see Warnings and Precautions (5.9)]

6.1 Clinical Trials Experience

Because clinical trials are conducted under widely varying conditions, adverse reaction rates observed in the clinical trials of a drug cannot be directly compared to rates in the clinical trials of another drug and may not reflect the rates observed in practice.

Postherpetic Neuralgia

The most common adverse reactions associated with the use of NEURONTIN in adults, not seen at an equivalent frequency among placebo-treated patients, were dizziness, somnolence, and peripheral edema.

In the 2 controlled trials in postherpetic neuralgia, 16% of the 336 patients who received NEURONTIN and 9% of the 227 patients who received placebo discontinued treatment because of an adverse reaction. The adverse reactions that most frequently led to withdrawal in NEURONTIN-treated patients were dizziness, somnolence, and nausea.

Table 3 lists adverse reactions that occurred in at least 1% of NEURONTIN-treated patients with postherpetic neuralgia participating in placebo-controlled trials and that were numerically more frequent in the NEURONTIN group than in the placebo group.

TABLE 3. Adverse Reactions in Pooled Placebo-Controlled Trials in Postherpetic Neuralgia
 | NEURONTIN; N=336; % | Placebo; N=227; %
Body as a Whole
Asthenia | 6 | 5
Infection | 5 | 4
Accidental injury | 3 | 1
Digestive System
Diarrhea | 6 | 3
Dry mouth | 5 | 1
Constipation | 4 | 2
Nausea | 4 | 3
Vomiting | 3 | 2
Metabolic and Nutritional Disorders
Peripheral edema | 8 | 2
Weight gain | 2 | 0
Hyperglycemia | 1 | 0
Nervous System
Dizziness | 28 | 8
Somnolence | 21 | 5
Ataxia | 3 | 0
Abnormal thinking | 3 | 0
Abnormal gait | 2 | 0
Incoordination | 2 | 0
Respiratory System
Pharyngitis | 1 | 0
Special Senses
Amblyopia [Reported as blurred vision] | 3 | 1
Conjunctivitis | 1 | 0
Diplopia | 1 | 0
Otitis media | 1 | 0

Other reactions in more than 1% of patients but equally or more frequent in the placebo group included pain, tremor, neuralgia, back pain, dyspepsia, dyspnea, and flu syndrome.

There were no clinically important differences between men and women in the types and incidence of adverse reactions. Because there were few patients whose race was reported as other than white, there are insufficient data to support a statement regarding the distribution of adverse reactions by race.

Epilepsy with Partial Onset Seizures (Adjunctive Therapy)

The most common adverse reactions with NEURONTIN in combination with other antiepileptic drugs in patients >12 years of age, not seen at an equivalent frequency among placebo-treated patients, were somnolence, dizziness, ataxia, fatigue, and nystagmus.

The most common adverse reactions with NEURONTIN in combination with other antiepileptic drugs in pediatric patients 3 to 12 years of age, not seen at an equal frequency among placebo-treated patients, were viral infection, fever, nausea and/or vomiting, somnolence, and hostility [see Warnings and Precautions (5.9)].

Approximately 7% of the 2074 patients >12 years of age and approximately 7% of the 449 pediatric patients 3 to 12 years of age who received NEURONTIN in premarketing clinical trials discontinued treatment because of an adverse reaction. The adverse reactions most commonly associated with withdrawal in patients >12 years of age were somnolence (1.2%), ataxia (0.8%), fatigue (0.6%), nausea and/or vomiting (0.6%), and dizziness (0.6%). The adverse reactions most commonly associated with withdrawal in pediatric patients were emotional lability (1.6%), hostility (1.3%), and hyperkinesia (1.1%).

Table 4 lists adverse reactions that occurred in at least 1% of NEURONTIN-treated patients >12 years of age with epilepsy participating in placebo-controlled trials and were numerically more common in the NEURONTIN group. In these studies, either NEURONTIN or placebo was added to the patient’s current antiepileptic drug therapy.

TABLE 4. Adverse Reactions in Pooled Placebo-Controlled Add-On Trials in Epilepsy Patients >12 Years of Age
 | NEURONTIN [Plus background antiepileptic drug therapy]; N=543; % | Placebo; N=378; %
Body as a Whole
Fatigue | 11 | 5
Increased weight | 3 | 2
Back pain | 2 | 1
Peripheral edema | 2 | 1
Cardiovascular
Vasodilatation | 1 | 0
Digestive System
Dyspepsia | 2 | 1
Dry mouth or throat | 2 | 1
Constipation | 2 | 1
Dental abnormalities | 2 | 0
Nervous System
Somnolence | 19 | 9
Dizziness | 17 | 7
Ataxia | 13 | 6
Nystagmus | 8 | 4
Tremor | 7 | 3
Dysarthria | 2 | 1
Amnesia | 2 | 0
Depression | 2 | 1
Abnormal thinking | 2 | 1
Abnormal coordination | 1 | 0
Respiratory System
Pharyngitis | 3 | 2
Coughing | 2 | 1
Skin and Appendages
Abrasion | 1 | 0
Urogenital System
Impotence | 2 | 1
Special Senses
Diplopia | 6 | 2
Amblyopia [Amblyopia was often described as blurred vision.] | 4 | 1

Among the adverse reactions occurring at an incidence of at least 10% in NEURONTIN-treated patients, somnolence and ataxia appeared to exhibit a positive dose-response relationship.

The overall incidence of adverse reactions and the types of adverse reactions seen were similar among men and women treated with NEURONTIN. The incidence of adverse reactions increased slightly with increasing age in patients treated with either NEURONTIN or placebo. Because only 3% of patients (28/921) in placebo-controlled studies were identified as nonwhite (black or other), there are insufficient data to support a statement regarding the distribution of adverse reactions by race.

Table 5 lists adverse reactions that occurred in at least 2% of NEURONTIN-treated patients, age 3 to 12 years of age with epilepsy participating in placebo-controlled trials, and which were numerically more common in the NEURONTIN group.

TABLE 5. Adverse Reactions in a Placebo-Controlled Add-On Trial in Pediatric Epilepsy Patients Age 3 to 12 Years
 | NEURONTIN [Plus background antiepileptic drug therapy]; N=119; % | Placebo; N=128; %
Body as a Whole
Viral infection | 11 | 3
Fever | 10 | 3
Increased weight | 3 | 1
Fatigue | 3 | 2
Digestive System
Nausea and/or vomiting | 8 | 7
Nervous System
Somnolence | 8 | 5
Hostility | 8 | 2
Emotional lability | 4 | 2
Dizziness | 3 | 2
Hyperkinesia | 3 | 1
Respiratory System
Bronchitis | 3 | 1
Respiratory infection | 3 | 1

Other reactions in more than 2% of pediatric patients 3 to 12 years of age but equally or more frequent in the placebo group included: pharyngitis, upper respiratory infection, headache, rhinitis, convulsions, diarrhea, anorexia, coughing, and otitis media.

6.2 Postmarketing Experience

The following adverse reactions have been identified during postmarketing use of NEURONTIN. Because these reactions are reported voluntarily from a population of uncertain size, it is not always possible to reliably estimate their frequency or establish a causal relationship to drug exposure.

Hepatobiliary Disorders: jaundice

Investigations: elevated creatine kinase, elevated liver function tests

Metabolism and Nutrition Disorders: hyponatremia

Musculoskeletal and Connective Tissue Disorder: rhabdomyolysis

Nervous System Disorders: movement disorder

Psychiatric Disorders: agitation

Reproductive System and Breast Disorders: breast enlargement, changes in libido, ejaculation disorders and anorgasmia

Skin and Subcutaneous Tissue Disorders: angioedema [see Warnings and Precautions (5.2)], bullous pemphigoid, erythema multiforme, Stevens-Johnson syndrome.

There are postmarketing reports of life-threatening or fatal respiratory depression in patients taking NEURONTIN with opioids or other CNS depressants, or in the setting of underlying respiratory impairment [see Warnings and Precautions (5.8)].

There are postmarketing reports of withdrawal symptoms after discontinuation of gabapentin. Reported adverse reactions include, but are not limited to, seizures, depression, suicidal ideation and behavior, agitation, confusion, disorientation, psychotic symptoms, anxiety, insomnia, nausea, pain, sweating, tremor, headache, dizziness, and malaise [see Warnings and Precautions (5.6)].

7 DRUG INTERACTIONS

7.1 Opioids

Respiratory depression and sedation, sometimes resulting in death, have been reported following coadministration of gabapentin with opioids (e.g., morphine, hydrocodone, oxycodone, buprenorphine) [see Warnings and Precautions (5.8)].

Hydrocodone

Coadministration of NEURONTIN with hydrocodone decreases hydrocodone exposure [see Clinical Pharmacology (12.3)]. The potential for alteration in hydrocodone exposure and effect should be considered when NEURONTIN is started or discontinued in a patient taking hydrocodone.

Morphine

When gabapentin is administered with morphine, patients should be observed for signs of CNS depression, such as somnolence, sedation and respiratory depression [see Clinical Pharmacology (12.3)].

7.2 Other Antiepileptic Drugs

Gabapentin is not appreciably metabolized nor does it interfere with the metabolism of commonly coadministered antiepileptic drugs [see Clinical Pharmacology (12.3)].

7.3 Maalox® (aluminum hydroxide, magnesium hydroxide)

The mean bioavailability of gabapentin was reduced by about 20% with concomitant use of an antacid (Maalox®) containing magnesium and aluminum hydroxides. It is recommended that gabapentin be taken at least 2 hours following Maalox administration [see Clinical Pharmacology (12.3)].

7.4 Drug/Laboratory Test Interactions

Because false positive readings were reported with the Ames N-Multistix SG® dipstick test for urinary protein when gabapentin was added to other antiepileptic drugs, the more specific sulfosalicylic acid precipitation procedure is recommended to determine the presence of urine protein.

8 USE IN SPECIFIC POPULATIONS

8.1 Pregnancy

Pregnancy Exposure Registry

There is a pregnancy exposure registry that monitors pregnancy outcomes in women exposed to antiepileptic drugs (AEDs), such as NEURONTIN, during pregnancy. Encourage women who are taking NEURONTIN during pregnancy to enroll in the North American Antiepileptic Drug (NAAED) Pregnancy Registry by calling the toll-free number 1-888-233-2334 or visiting http://www.aedpregnancyregistry.org/.

Risk Summary

The totality of available data from published prospective and retrospective cohort studies pertaining to gabapentin use during pregnancy has not indicated an increased risk of major birth defects or miscarriage. There are important methodological limitations hindering interpretation of these studies [see Data]. In nonclinical studies in mice, rats, and rabbits, gabapentin was developmentally toxic (increased fetal skeletal and visceral abnormalities, and increased embryofetal mortality) when administered to pregnant animals at doses similar to or lower than those used clinically [see Data].

Postmarketing data suggest that extended gabapentin use with opioids close to delivery may increase the risk of neonatal withdrawal versus opioids alone [see Clinical Considerations]. Although there is at least one report of neonatal withdrawal syndrome in an infant exposed to gabapentin alone during pregnancy, there are no comparative epidemiologic studies evaluating this association. Therefore, whether exposure to gabapentin alone late in pregnancy may cause withdrawal signs and symptoms is not known.

The background risk of major birth defects and miscarriage for the indicated population is unknown. All pregnancies have a background risk of birth defect, loss, or other adverse outcomes. In the U.S. general population, the estimated background risk of major birth defects and miscarriage in clinically recognized pregnancies is 2 to 4% and 15 to 20%, respectively.

Clinical Considerations

Fetal/Neonatal Adverse Reactions

Neonatal withdrawal syndrome has been reported in newborns exposed to gabapentin in utero for an extended period of time when also exposed to opioids close to delivery. Neonatal withdrawal signs and symptoms reported have included tachypnea, vomiting, diarrhea, hypertonia, irritability, sneezing, poor feeding, hyperactivity, abnormal sleep pattern, and tremor. Reported signs and symptoms that may also be related to withdrawal include tongue thrusting, wandering eye movements while awake, back arching, and continuous extremity movements. Observe neonates exposed to NEURONTIN and opioids for signs and symptoms of neonatal withdrawal and manage accordingly.

Data

Human Data

An observational study based on routinely collected data from administrative and medical registers in Denmark, Finland, Norway, and Sweden, compared the prevalence of major congenital malformations in approximately 1,500 pregnancies exposed to gabapentin monotherapy in the first trimester to pregnancies unexposed to antiepileptics (n=2,995,816) and pregnancies exposed to lamotrigine monotherapy in the first trimester (n=7,582). The adjusted prevalence ratios in a pooled analysis were 1.00 (95% CI: 0.80-1.24) compared to pregnancies unexposed to antiepileptics and 1.29 (95% CI: 1.00-1.67) compared to pregnancies exposed to lamotrigine monotherapy in the first trimester.

Data from another observational study in the US based on Medicaid data, which compared the risk for major congenital malformations in more than 4,600 pregnancies exposed to gabapentin during the first trimester to unexposed pregnancies (n=1,753,865), estimated an adjusted relative risk of 1.07 (95% CI: 0.94-1.21).

Data from a cohort study of over 200,000 Medicaid-eligible pregnancies with prescription opioid exposure in the last 45 days of pregnancy found that the risk of neonatal drug withdrawal was greater in pregnancies with combined exposure to gabapentin and opioids compared to pregnancies with exposure to opioids alone.

The data from these observational studies should be interpreted with caution due to the potential for exposure misclassification, outcome misclassification, and residual confounding, including by underlying disease.

Animal Data

When pregnant mice received oral doses of gabapentin (500, 1000, or 3000 mg/kg/day) during the period of organogenesis, embryofetal toxicity (increased incidences of skeletal variations) was observed at the two highest doses. The no-effect dose for embryofetal developmental toxicity in mice (500 mg/kg/day) is less than the maximum recommended human dose (MRHD) of 3600 mg on a body surface area (mg/m^2) basis.

In studies in which rats received oral doses of gabapentin (500 to 2000 mg/kg/day) during pregnancy, adverse effect on offspring development (increased incidences of hydroureter and/or hydronephrosis) were observed at all doses. The lowest dose tested is similar to the MRHD on a mg/m^2 basis.

When pregnant rabbits were treated with gabapentin during the period of organogenesis, an increase in embryofetal mortality was observed at all doses tested (60, 300, or 1500 mg/kg). The lowest dose tested is less than the MRHD on a mg/m^2 basis.

In a published study, gabapentin (400 mg/kg/day) was administered by intraperitoneal injection to neonatal mice during the first postnatal week, a period of synaptogenesis in rodents (corresponding to the last trimester of pregnancy in humans). Gabapentin caused a marked decrease in neuronal synapse formation in brains of intact mice and abnormal neuronal synapse formation in a mouse model of synaptic repair. Gabapentin has been shown in vitro to interfere with activity of the α2δ subunit of voltage-activated calcium channels, a receptor involved in neuronal synaptogenesis. The clinical significance of these findings is unknown.

8.2 Lactation

Risk Summary

Gabapentin is secreted in human milk following oral administration. The effects on the breastfed infant and on milk production are unknown. The developmental and health benefits of breastfeeding should be considered along with the mother's clinical need for NEURONTIN and any potential adverse effects on the breastfed infant from NEURONTIN or from the underlying maternal condition.

8.4 Pediatric Use

Safety and effectiveness of NEURONTIN in the management of postherpetic neuralgia in pediatric patients have not been established.

Safety and effectiveness as adjunctive therapy in the treatment of partial seizures in pediatric patients below the age of 3 years has not been established [see Clinical Studies (14.2)].

8.5 Geriatric Use

The total number of patients treated with NEURONTIN in controlled clinical trials in patients with postherpetic neuralgia was 336, of which 102 (30%) were 65 to 74 years of age, and 168 (50%) were 75 years of age and older. There was a larger treatment effect in patients 75 years of age and older compared to younger patients who received the same dosage. Since gabapentin is almost exclusively eliminated by renal excretion, the larger treatment effect observed in patients ≥75 years may be a consequence of increased gabapentin exposure for a given dose that results from an age-related decrease in renal function. However, other factors cannot be excluded. The types and incidence of adverse reactions were similar across age groups except for peripheral edema and ataxia, which tended to increase in incidence with age.

Clinical studies of NEURONTIN in epilepsy did not include sufficient numbers of subjects aged 65 and over to determine whether they responded differently from younger subjects. Other reported clinical experience has not identified differences in responses between the elderly and younger patients. In general, dose selection for an elderly patient should be cautious, usually starting at the low end of the dosing range, reflecting the greater frequency of decreased hepatic, renal, or cardiac function, and of concomitant disease or other drug therapy.

This drug is known to be substantially excreted by the kidney, and the risk of toxic reactions to this drug may be greater in patients with impaired renal function. Because elderly patients are more likely to have decreased renal function, care should be taken in dose selection, and dose should be adjusted based on creatinine clearance values in these patients [see Dosage and Administration (2.4), Adverse Reactions (6), and Clinical Pharmacology (12.3)].

8.6 Renal Impairment

Dosage adjustment in adult patients with compromised renal function is necessary [see Dosage and Administration (2.3) and Clinical Pharmacology (12.3)]. Pediatric patients with renal insufficiency have not been studied.

Dosage adjustment in patients undergoing hemodialysis is necessary [see Dosage and Administration (2.3) and Clinical Pharmacology (12.3)].

9 DRUG ABUSE AND DEPENDENCE

9.1 Controlled Substance

NEURONTIN contains gabapentin, which is not a controlled substance.

9.2 Abuse

Abuse is the intentional, non-therapeutic use of a drug, even once, for its desirable psychological or physiological effects. Misuse is the intentional use, for therapeutic purposes, of a drug by an individual in a way other than prescribed by a health care provider or for whom it was not prescribed.

Gabapentin does not exhibit affinity for benzodiazepine, opioid (mu, delta or kappa), or cannabinoid 1 receptor sites. Gabapentin misuse and abuse have been reported in the postmarketing setting and published literature. Most of the individuals described in these reports had a history of polysubstance abuse. Some of these individuals were taking higher than recommended doses of gabapentin for unapproved uses. When prescribing NEURONTIN, carefully evaluate patients for a history of drug abuse and observe them for signs and symptoms of gabapentin misuse or abuse (e.g., self-dose escalation and drug-seeking behavior). The abuse potential of gabapentin has not been evaluated in human studies.

9.3 Dependence

Physical dependence is a state that develops as a result of physiological adaptation in response to repeated drug use, manifested by withdrawal signs and symptoms after abrupt discontinuation or a significant dose reduction of a drug.

After discontinuation of short-term and long-term treatment with gabapentin, withdrawal symptoms have been observed in some patients. Withdrawal symptoms may occur shortly after discontinuation, usually within 48 hours. In the postmarketing setting, reported adverse reactions have included, but not been limited to, seizures, depression, suicidal ideation and behavior, agitation, confusion, disorientation, psychotic symptoms, anxiety, insomnia, nausea, pain, sweating, tremor, headache, dizziness, and malaise. The dependence potential of gabapentin has not been evaluated in human studies.

10 OVERDOSAGE

Signs of acute toxicity in animals included ataxia, labored breathing, ptosis, sedation, hypoactivity, or excitation.

Acute oral overdoses of NEURONTIN have been reported. Symptoms have included double vision, tremor, slurred speech, drowsiness, altered mental status, dizziness, lethargy, and diarrhea. Fatal respiratory depression has been reported with NEURONTIN overdose, alone and in combination with other CNS depressants.

Gabapentin can be removed by hemodialysis.

If overexposure occurs, call your poison control center at 1-800-222-1222.

11 DESCRIPTION

The active ingredient in NEURONTIN capsules, tablets, and oral solution is gabapentin, which has the chemical name 1-(aminomethyl)cyclohexaneacetic acid.

The molecular formula of gabapentin is C9H17NO2 and the molecular weight is 171.24. The structural formula of gabapentin is:

Gabapentin is a white to off-white crystalline solid with a pKa1 of 3.7 and a pKa2 of 10.7. It is freely soluble in water and both basic and acidic aqueous solutions. The log of the partition coefficient (n-octanol/0.05M phosphate buffer) at pH 7.4 is -1.25.

Each NEURONTIN capsule contains 100 mg, 300 mg, or 400 mg of gabapentin and the following inactive ingredients: cornstarch, FD&C Blue No. 2, gelatin, lactose, red iron oxide (400 mg only), talc, titanium dioxide, and yellow iron oxide (300 mg and 400 mg only).

Each NEURONTIN tablet contains 600 mg or 800 mg of gabapentin and the following inactive ingredients: candelilla wax, copovidone, cornstarch, hydroxypropyl cellulose, magnesium stearate, poloxamer 407, and talc.

NEURONTIN oral solution contains 250 mg of gabapentin per 5 mL (50 mg per mL) and the following inactive ingredients: artificial cool strawberry anise flavor, glycerin, purified water, and xylitol.

12 CLINICAL PHARMACOLOGY

12.1 Mechanism of Action

The precise mechanisms by which gabapentin produces its analgesic and antiepileptic actions are unknown. Gabapentin is structurally related to the neurotransmitter gamma-aminobutyric acid (GABA) but has no effect on GABA binding, uptake, or degradation. In vitro studies have shown that gabapentin binds with high-affinity to the α2δ subunit of voltage-activated calcium channels; however, the relationship of this binding to the therapeutic effects of gabapentin is unknown.

12.3 Pharmacokinetics

All pharmacological actions following gabapentin administration are due to the activity of the parent compound; gabapentin is not appreciably metabolized in humans.

Oral Bioavailability

Gabapentin bioavailability is not dose proportional; i.e., as dose is increased, bioavailability decreases. Bioavailability of gabapentin is approximately 60%, 47%, 34%, 33%, and 27% following 900, 1200, 2400, 3600, and 4800 mg/day given in 3 divided doses, respectively. Food has only a slight effect on the rate and extent of absorption of gabapentin (14% increase in AUC and Cmax).

Distribution

Less than 3% of gabapentin circulates bound to plasma protein. The apparent volume of distribution of gabapentin after 150 mg intravenous administration is 58±6 L (mean ±SD). In patients with epilepsy, steady-state predose (Cmin) concentrations of gabapentin in cerebrospinal fluid were approximately 20% of the corresponding plasma concentrations.

Elimination

Gabapentin is eliminated from the systemic circulation by renal excretion as unchanged drug. Gabapentin is not appreciably metabolized in humans.

Gabapentin elimination half-life is 5 to 7 hours and is unaltered by dose or following multiple dosing. Gabapentin elimination rate constant, plasma clearance, and renal clearance are directly proportional to creatinine clearance. In elderly patients, and in patients with impaired renal function, gabapentin plasma clearance is reduced. Gabapentin can be removed from plasma by hemodialysis.

Specific Populations

Age

The effect of age was studied in subjects 20-80 years of age. Apparent oral clearance (CL/F) of gabapentin decreased as age increased, from about 225 mL/min in those under 30 years of age to about 125 mL/min in those over 70 years of age. Renal clearance (CLr) and CLr adjusted for body surface area also declined with age; however, the decline in the renal clearance of gabapentin with age can largely be explained by the decline in renal function. [see Dosage and Administration (2.4) and Use in Specific Populations (8.5)].

Gender

Although no formal study has been conducted to compare the pharmacokinetics of gabapentin in men and women, it appears that the pharmacokinetic parameters for males and females are similar and there are no significant gender differences.

Race

Pharmacokinetic differences due to race have not been studied. Because gabapentin is primarily renally excreted and there are no important racial differences in creatinine clearance, pharmacokinetic differences due to race are not expected.

Pediatric

Gabapentin pharmacokinetics were determined in 48 pediatric subjects between the ages of 1 month and 12 years following a dose of approximately 10 mg/kg. Peak plasma concentrations were similar across the entire age group and occurred 2 to 3 hours postdose. In general, pediatric subjects between 1 month and <5 years of age achieved approximately 30% lower exposure (AUC) than that observed in those 5 years of age and older. Accordingly, oral clearance normalized per body weight was higher in the younger children. Apparent oral clearance of gabapentin was directly proportional to creatinine clearance. Gabapentin elimination half-life averaged 4.7 hours and was similar across the age groups studied.

A population pharmacokinetic analysis was performed in 253 pediatric subjects between 1 month and 13 years of age. Patients received 10 to 65 mg/kg/day given three times a day. Apparent oral clearance (CL/F) was directly proportional to creatinine clearance and this relationship was similar following a single dose and at steady-state. Higher oral clearance values were observed in children <5 years of age compared to those observed in children 5 years of age and older, when normalized per body weight. The clearance was highly variable in infants <1 year of age. The normalized CL/F values observed in pediatric patients 5 years of age and older were consistent with values observed in adults after a single dose. The oral volume of distribution normalized per body weight was constant across the age range.

These pharmacokinetic data indicate that the effective daily dose in pediatric patients with epilepsy ages 3 and 4 years should be 40 mg/kg/day to achieve average plasma concentrations similar to those achieved in patients 5 years of age and older receiving gabapentin at 30 mg/kg/day [see Dosage and Administration (2.2)].

Adult Patients with Renal Impairment

Subjects (N=60) with renal impairment (mean creatinine clearance ranging from 13-114 mL/min) were administered single 400 mg oral doses of gabapentin. The mean gabapentin half-life ranged from about 6.5 hours (patients with creatinine clearance >60 mL/min) to 52 hours (creatinine clearance <30 mL/min) and gabapentin renal clearance from about 90 mL/min (>60 mL/min group) to about 10 mL/min (<30 mL/min). Mean plasma clearance (CL/F) decreased from approximately 190 mL/min to 20 mL/min [see Dosage and Administration (2.3) and Use in Specific Populations (8.6)]. Pediatric patients with renal insufficiency have not been studied.

Hemodialysis

In a study in anuric adult subjects (N=11), the apparent elimination half-life of gabapentin on nondialysis days was about 132 hours; during dialysis the apparent half-life of gabapentin was reduced to 3.8 hours. Hemodialysis thus has a significant effect on gabapentin elimination in anuric subjects [see Dosage and Administration (2.3) and Use in Specific Populations (8.6)].

Hepatic Disease

Because gabapentin is not metabolized, no study was performed in patients with hepatic impairment.

Drug Interactions

- In Vitro Studies
  In vitro studies were conducted to investigate the potential of gabapentin to inhibit the major cytochrome P450 enzymes (CYP1A2, CYP2A6, CYP2C9, CYP2C19, CYP2D6, CYP2E1, and CYP3A4) that mediate drug and xenobiotic metabolism using isoform selective marker substrates and human liver microsomal preparations. Only at the highest concentration tested (171 mcg/mL; 1 mM) was a slight degree of inhibition (14% to 30%) of isoform CYP2A6 observed. No inhibition of any of the other isoforms tested was observed at gabapentin concentrations up to 171 mcg/mL (approximately 15 times the Cmax at 3600 mg/day).
- In Vivo Studies
  The drug interaction data described in this section were obtained from studies involving healthy adults and adult patients with epilepsy.
  Phenytoin
  In a single (400 mg) and multiple dose (400 mg three times a day) study of NEURONTIN in epileptic patients (N=8) maintained on phenytoin monotherapy for at least 2 months, gabapentin had no effect on the steady-state trough plasma concentrations of phenytoin and phenytoin had no effect on gabapentin pharmacokinetics.
  Carbamazepine
  Steady-state trough plasma carbamazepine and carbamazepine 10, 11 epoxide concentrations were not affected by concomitant gabapentin (400 mg three times a day; N=12) administration. Likewise, gabapentin pharmacokinetics were unaltered by carbamazepine administration.
  Valproic Acid
  The mean steady-state trough serum valproic acid concentrations prior to and during concomitant gabapentin administration (400 mg three times a day; N=17) were not different and neither were gabapentin pharmacokinetic parameters affected by valproic acid.
  Phenobarbital
  Estimates of steady-state pharmacokinetic parameters for phenobarbital or gabapentin (300 mg three times a day; N=12) are identical whether the drugs are administered alone or together.
  Naproxen
  Coadministration (N=18) of naproxen sodium capsules (250 mg) with NEURONTIN (125 mg) appears to increase the amount of gabapentin absorbed by 12% to 15%. Gabapentin had no effect on naproxen pharmacokinetic parameters. These doses are lower than the therapeutic doses for both drugs. The magnitude of interaction within the recommended dose ranges of either drug is not known.
  Hydrocodone
  Coadministration of NEURONTIN (125 to 500 mg; N=48) decreases hydrocodone (10 mg; N=50) Cmax and AUC values in a dose-dependent manner relative to administration of hydrocodone alone; Cmax and AUC values are 3% to 4% lower, respectively, after administration of 125 mg NEURONTIN and 21% to 22% lower, respectively, after administration of 500 mg NEURONTIN. The mechanism for this interaction is unknown. Hydrocodone increases gabapentin AUC values by 14%. The magnitude of interaction at other doses is not known.
  Morphine
  A literature article reported that when a 60 mg controlled-release morphine capsule was administered 2 hours prior to a 600 mg NEURONTIN capsule (N=12), mean gabapentin AUC increased by 44% compared to gabapentin administered without morphine. Morphine pharmacokinetic parameter values were not affected by administration of NEURONTIN 2 hours after morphine. The magnitude of interaction at other doses is not known.
  Cimetidine
  In the presence of cimetidine at 300 mg four times a day (N=12), the mean apparent oral clearance of gabapentin fell by 14% and creatinine clearance fell by 10%. Thus, cimetidine appeared to alter the renal excretion of both gabapentin and creatinine, an endogenous marker of renal function. This decrease in excretion of gabapentin by cimetidine is not expected to be of clinical importance. The effect of gabapentin on cimetidine was not evaluated.
  Oral Contraceptive
  Based on AUC and half-life, multiple-dose pharmacokinetic profiles of norethindrone and ethinyl estradiol following administration of tablets containing 2.5 mg of norethindrone acetate and 50 mcg of ethinyl estradiol were similar with and without coadministration of gabapentin (400 mg three times a day; N=13). The Cmax of norethindrone was 13% higher when it was coadministered with gabapentin; this interaction is not expected to be of clinical importance.
  Antacid (Maalox®) (aluminum hydroxide, magnesium hydroxide)
  Antacid (Maalox®) containing magnesium and aluminum hydroxides reduced the mean bioavailability of gabapentin (N=16) by about 20%. This decrease in bioavailability was about 10% when gabapentin was administered 2 hours after Maalox.
  Probenecid
  Probenecid is a blocker of renal tubular secretion. Gabapentin pharmacokinetic parameters without and with probenecid were comparable. This indicates that gabapentin does not undergo renal tubular secretion by the pathway that is blocked by probenecid.

13 NONCLINICAL TOXICOLOGY

13.1 Carcinogenesis, Mutagenesis, Impairment of Fertility

Carcinogenesis

Gabapentin was administered orally to mice and rats in 2-year carcinogenicity studies. No evidence of drug-related carcinogenicity was observed in mice treated at doses up to 2000 mg/kg/day. At 2000 mg/kg, the plasma gabapentin exposure (AUC) in mice was approximately 2 times that in humans at the MRHD of 3600 mg/day. In rats, increases in the incidence of pancreatic acinar cell adenoma and carcinoma were found in male rats receiving the highest dose (2000 mg/kg), but not at doses of 250 or 1000 mg/kg/day. At 1000 mg/kg, the plasma gabapentin exposure (AUC) in rats was approximately 5 times that in humans at the MRHD.

Studies designed to investigate the mechanism of gabapentin-induced pancreatic carcinogenesis in rats indicate that gabapentin stimulates DNA synthesis in rat pancreatic acinar cells in vitro and, thus, may be acting as a tumor promoter by enhancing mitogenic activity. It is not known whether gabapentin has the ability to increase cell proliferation in other cell types or in other species, including humans.

Mutagenesis

Gabapentin did not demonstrate mutagenic or genotoxic potential in in vitro (Ames test, HGPRT forward mutation assay in Chinese hamster lung cells) and in vivo (chromosomal aberration and micronucleus test in Chinese hamster bone marrow, mouse micronucleus, unscheduled DNA synthesis in rat hepatocytes) assays.

Impairment of Fertility

No adverse effects on fertility or reproduction were observed in rats at doses up to 2000 mg/kg. At 2000 mg/kg, the plasma gabapentin exposure (AUC) in rats is approximately 8 times that in humans at the MRHD.

14 CLINICAL STUDIES

14.1 Postherpetic Neuralgia

NEURONTIN was evaluated for the management of postherpetic neuralgia (PHN) in two randomized, double-blind, placebo-controlled, multicenter studies. The intent-to-treat (ITT) population consisted of a total of 563 patients with pain for more than 3 months after healing of the herpes zoster skin rash (Table 6).

TABLE 6. Controlled PHN Studies: Duration, Dosages, and Number of Patients
Study | Study; Duration | Gabapentin; (mg/day) [Given in 3 divided doses (TID)]; Target Dose | Patients; Receiving; Gabapentin | Patients; Receiving; Placebo
1 | 8 weeks | 3600 | 113 | 116
2 | 7 weeks | 1800, 2400 | 223 | 111
Total |  |  | 336 | 227

Each study included a 7- or 8-week double-blind phase (3 or 4 weeks of titration and 4 weeks of fixed dose). Patients initiated treatment with titration to a maximum of 900 mg/day gabapentin over 3 days. Dosages were then to be titrated in 600 to 1200 mg/day increments at 3- to 7-day intervals to the target dose over 3 to 4 weeks. Patients recorded their pain in a daily diary using an 11-point numeric pain rating scale ranging from 0 (no pain) to 10 (worst possible pain). A mean pain score during baseline of at least 4 was required for randomization. Analyses were conducted using the ITT population (all randomized patients who received at least one dose of study medication).

Both studies demonstrated efficacy compared to placebo at all doses tested.

The reduction in weekly mean pain scores was seen by Week 1 in both studies, and were maintained to the end of treatment. Comparable treatment effects were observed in all active treatment arms. Pharmacokinetic/pharmacodynamic modeling provided confirmatory evidence of efficacy across all doses. Figures 1 and 2 show pain intensity scores over time for Studies 1 and 2.

Figure 1. Weekly Mean Pain Scores (Observed Cases in ITT Population): Study 1
Figure 2. Weekly Mean Pain Scores (Observed Cases in ITT Population): Study 2

The proportion of responders (those patients reporting at least 50% improvement in endpoint pain score compared to baseline) was calculated for each study (Figure 3).

Figure 3. Proportion of Responders (patients with ≥50% reduction in pain score) at Endpoint: Controlled PHN Studies

14.2 Epilepsy for Partial Onset Seizures (Adjunctive Therapy)

The effectiveness of NEURONTIN as adjunctive therapy (added to other antiepileptic drugs) was established in multicenter placebo-controlled, double-blind, parallel-group clinical trials in adult and pediatric patients (3 years and older) with refractory partial seizures.

Evidence of effectiveness was obtained in three trials conducted in 705 patients (age 12 years and above) and one trial conducted in 247 pediatric patients (3 to 12 years of age). The patients enrolled had a history of at least 4 partial seizures per month in spite of receiving one or more antiepileptic drugs at therapeutic levels and were observed on their established antiepileptic drug regimen during a 12-week baseline period (6 weeks in the study of pediatric patients). In patients continuing to have at least 2 (or 4 in some studies) seizures per month, NEURONTIN or placebo was then added on to the existing therapy during a 12-week treatment period. Effectiveness was assessed primarily on the basis of the percent of patients with a 50% or greater reduction in seizure frequency from baseline to treatment (the “responder rate”) and a derived measure called response ratio, a measure of change defined as (T - B)/(T + B), in which B is the patient’s baseline seizure frequency and T is the patient’s seizure frequency during treatment. Response ratio is distributed within the range -1 to +1. A zero value indicates no change while complete elimination of seizures would give a value of -1; increased seizure rates would give positive values. A response ratio of -0.33 corresponds to a 50% reduction in seizure frequency. The results given below are for all partial seizures in the intent-to-treat (all patients who received any doses of treatment) population in each study, unless otherwise indicated.

One study compared NEURONTIN 1200 mg/day, in three divided doses with placebo. Responder rate was 23% (14/61) in the NEURONTIN group and 9% (6/66) in the placebo group; the difference between groups was statistically significant. Response ratio was also better in the NEURONTIN group (-0.199) than in the placebo group (-0.044), a difference that also achieved statistical significance.

A second study compared primarily NEURONTIN 1200 mg/day, in three divided doses (N=101), with placebo (N=98). Additional smaller NEURONTIN dosage groups (600 mg/day, N=53; 1800 mg/day, N=54) were also studied for information regarding dose response. Responder rate was higher in the NEURONTIN 1200 mg/day group (16%) than in the placebo group (8%), but the difference was not statistically significant. The responder rate at 600 mg (17%) was also not significantly higher than in the placebo, but the responder rate in the 1800 mg group (26%) was statistically significantly superior to the placebo rate. Response ratio was better in the NEURONTIN 1200 mg/day group (-0.103) than in the placebo group (-0.022); but this difference was also not statistically significant (p = 0.224). A better response was seen in the NEURONTIN 600 mg/day group (-0.105) and 1800 mg/day group (-0.222) than in the 1200 mg/day group, with the 1800 mg/day group achieving statistical significance compared to the placebo group.

A third study compared NEURONTIN 900 mg/day, in three divided doses (N=111), and placebo (N=109). An additional NEURONTIN 1200 mg/day dosage group (N=52) provided dose-response data. A statistically significant difference in responder rate was seen in the NEURONTIN 900 mg/day group (22%) compared to that in the placebo group (10%). Response ratio was also statistically significantly superior in the NEURONTIN 900 mg/day group (-0.119) compared to that in the placebo group (-0.027), as was response ratio in 1200 mg/day NEURONTIN (-0.184) compared to placebo.

Analyses were also performed in each study to examine the effect of NEURONTIN on preventing secondarily generalized tonic-clonic seizures. Patients who experienced a secondarily generalized tonic-clonic seizure in either the baseline or in the treatment period in all three placebo-controlled studies were included in these analyses. There were several response ratio comparisons that showed a statistically significant advantage for NEURONTIN compared to placebo and favorable trends for almost all comparisons.

Analysis of responder rate using combined data from all three studies and all doses (N=162, NEURONTIN; N=89, placebo) also showed a significant advantage for NEURONTIN over placebo in reducing the frequency of secondarily generalized tonic-clonic seizures.

In two of the three controlled studies, more than one dose of NEURONTIN was used. Within each study, the results did not show a consistently increased response to dose. However, looking across studies, a trend toward increasing efficacy with increasing dose is evident (see Figure 4).

Figure 4. Responder Rate in Patients Receiving NEURONTIN Expressed as a Difference from Placebo by Dose and Study: Adjunctive Therapy Studies in Patients ≥12 Years of Age with Partial Seizures

In the figure, treatment effect magnitude, measured on the Y axis in terms of the difference in the proportion of gabapentin and placebo-assigned patients attaining a 50% or greater reduction in seizure frequency from baseline, is plotted against the daily dose of gabapentin administered (X axis).

Although no formal analysis by gender has been performed, estimates of response (Response Ratio) derived from clinical trials (398 men, 307 women) indicate no important gender differences exist. There was no consistent pattern indicating that age had any effect on the response to NEURONTIN. There were insufficient numbers of patients of races other than Caucasian to permit a comparison of efficacy among racial groups.

A fourth study in pediatric patients age 3 to 12 years compared 25-35 mg/kg/day NEURONTIN (N=118) with placebo (N=127). For all partial seizures in the intent-to-treat population, the response ratio was statistically significantly better for the NEURONTIN group (-0.146) than for the placebo group (-0.079). For the same population, the responder rate for NEURONTIN (21%) was not significantly different from placebo (18%).

A study in pediatric patients age 1 month to 3 years compared 40 mg/kg/day NEURONTIN (N=38) with placebo (N=38) in patients who were receiving at least one marketed antiepileptic drug and had at least one partial seizure during the screening period (within 2 weeks prior to baseline). Patients had up to 48 hours of baseline and up to 72 hours of double-blind video EEG monitoring to record and count the occurrence of seizures. There were no statistically significant differences between treatments in either the response ratio or responder rate.

16 HOW SUPPLIED/STORAGE AND HANDLING

NEURONTIN (gabapentin) capsules, tablets, and oral solution are supplied as follows:

100 mg capsules:

White hard gelatin capsules printed with “VLE” on the body and “Neurontin/100 mg” on the cap; available in:
Bottles of 100: NDC 58151-281-01

300 mg capsules:

Yellow hard gelatin capsules printed with “VLE” on the body and “Neurontin/300 mg” on the cap; available in:
Bottles of 100: NDC 58151-282-01

400 mg capsules:

Orange hard gelatin capsules printed with “VLE” on the body and “Neurontin/400 mg” on the cap; available in:
Bottles of 100: NDC 58151-283-01

600 mg tablets:

White elliptical film-coated scored tablets debossed with “NT” and “16” on one side; available in:
Bottles of 100: NDC 58151-284-01

800 mg tablets:

White elliptical film-coated scored tablets debossed with “NT” and “26” on one side; available in:
Bottles of 100: NDC 58151-285-01

250 mg per 5 mL oral solution:

Clear colorless to slightly yellow solution; each 5 mL of oral solution contains 250 mg of gabapentin; available in:
Bottles containing 470 mL: NDC 58151-290-35

Store NEURONTIN Tablets and Capsules at 25°C (77°F); excursions permitted between 15°C to 30°C (59°F to 86°F) [see USP Controlled Room Temperature].

Store NEURONTIN Oral Solution refrigerated, 2°C to 8°C (36°F to 46°F).

17 PATIENT COUNSELING INFORMATION

Advise the patient to read the FDA-approved patient labeling (Medication Guide).

Administration Information

Inform patients that NEURONTIN is taken orally with or without food. Inform patients that, should they divide the scored 600 mg or 800 mg tablet in order to administer a half-tablet, they should take the unused half-tablet as the next dose. Advise patients to discard half-tablets not used within 28 days of dividing the scored tablet.

Drug Reaction with Eosinophilia and Systemic Symptoms (DRESS)/Multiorgan Hypersensitivity

Prior to initiation of treatment with NEURONTIN, instruct patients that a rash or other signs or symptoms of hypersensitivity (such as fever or lymphadenopathy) may herald a serious medical event and that the patient should report any such occurrence to a healthcare provider immediately [see Warnings and Precautions (5.1)].

Anaphylaxis and Angioedema

Advise patients to discontinue NEURONTIN and seek medical care if they develop signs or symptoms of anaphylaxis or angioedema [see Warnings and Precautions (5.2)].

Dizziness and Somnolence and Effects on Driving and Operating Heavy Machinery

Advise patients that NEURONTIN may cause dizziness, somnolence, and other symptoms and signs of CNS depression. Other drugs with sedative properties may increase these symptoms. Accordingly, although patients’ ability to determine their level of impairment can be unreliable, advise them neither to drive a car nor to operate other complex machinery until they have gained sufficient experience on NEURONTIN to gauge whether or not it affects their mental and/or motor performance adversely. Inform patients that it is not known how long this effect lasts [see Warnings and Precautions (5.3) and Warnings and Precautions (5.4)].

Suicidal Thinking and Behavior

Counsel the patient, their caregivers, and families that AEDs, including NEURONTIN, may increase the risk of suicidal thoughts and behavior. Advise patients of the need to be alert for the emergence or worsening of symptoms of depression, any unusual changes in mood or behavior, or the emergence of suicidal thoughts, behavior, or thoughts about self-harm. Instruct patients to report behaviors of concern immediately to healthcare providers [see Warnings and Precautions (5.5)]. Also, inform patients who plan to or have discontinued NEURONTIN that suicidal thoughts and behavior can appear even after the drug is stopped.

Respiratory Depression

Inform patients about the risk of respiratory depression. Include information that the risk is greatest for those using concomitant CNS depressants (such as opioid analgesics) or those with underlying respiratory impairment. Teach patients how to recognize respiratory depression and advise them to seek medical attention immediately if it occurs [see Warnings and Precautions (5.8)].

Use in Pregnancy

Instruct patients to notify their healthcare provider if they are pregnant or intend to become pregnant during therapy, and to notify their healthcare provider if they are breast feeding or intend to breast feed during therapy [see Use in Specific Populations (8.1) and (8.2)].

Encourage patients to enroll in the NAAED Pregnancy Registry if they become pregnant. This registry is collecting information about the safety of antiepileptic drugs during pregnancy. To enroll, patients can call the toll-free number 1-888-233-2334 [see Use in Specific Populations (8.1)].

Distributed by:
Viatris Specialty LLC
Morgantown, WV 26505 U.S.A.

© 2025 Viatris Inc.

NEURONTIN is a registered trademark of UPJOHN US 1 LLC, a Viatris Company.

The brands listed are trademarks of their respective owners.

UPJ:NRTNCTOS:R2

Medication Guide

NEURONTIN (neu-RON-tin)

(gabapentin)

capsules, for oral use

NEURONTIN (neu-RON-tin)

(gabapentin)

tablets, for oral use
NEURONTIN (neu-RON-tin)

(gabapentin)

oral solution

What is the most important information I should know about NEURONTIN?

Do not stop taking NEURONTIN without first talking to your healthcare provider.

Stopping NEURONTIN suddenly can cause serious problems.

NEURONTIN can cause serious side effects including:

1. Suicidal Thoughts. Like other antiepileptic drugs, NEURONTIN may cause suicidal thoughts or actions in a very small number of people, about 1 in 500. This can happen while you take NEURONTIN as well as after stopping NEURONTIN.
  Call a healthcare provider right away if you have any of these symptoms, especially if they are new, worse, or worry you:
2. thoughts about suicide or dying
3. attempts to commit suicide
4. new or worse depression
5. new or worse anxiety
6. feeling agitated or restless
7. panic attacks
8. trouble sleeping (insomnia)
9. new or worse irritability
10. acting aggressive, being angry, or violent
11. acting on dangerous impulses
12. an extreme increase in activity and talking (mania)
13. other unusual changes in behavior or mood
How can I watch for early symptoms of suicidal thoughts and actions?
15. Pay attention to any changes, especially sudden changes, in mood, behaviors, thoughts, or feelings.
16. Keep all follow-up visits with your healthcare provider as scheduled.
Call your healthcare provider between visits as needed, especially if you are worried about symptoms.
Do not stop taking NEURONTIN without first talking to a healthcare provider.
19. Stopping NEURONTIN suddenly can cause serious problems. Stopping a seizure medicine suddenly in a person who has epilepsy can cause seizures that will not stop (status epilepticus).
20. Suicidal thoughts or actions can be caused by things other than medicines. If you have suicidal thoughts or actions, your healthcare provider may check for other causes.
2. Changes in behavior and thinking. Using NEURONTIN in children 3 to 12 years of age can cause emotional changes, aggressive behavior, problems with concentration, changes in school performance, restlessness, and hyperactivity.
3. NEURONTIN may cause serious or life-threatening allergic reactions that may affect your skin or other parts of your body such as your liver or blood cells. This may cause you to be hospitalized or to stop NEURONTIN. You may or may not have a rash with an allergic reaction caused by NEURONTIN. Call a healthcare provider right away if you have any of the following symptoms:
23. skin rash
24. hives
25. difficulty breathing
26. fever
27. swollen glands that do not go away
28. swelling of your face, lips, throat, or tongue
29. yellowing of your skin or of the whites of the eyes
30. unusual bruising or bleeding
31. severe fatigue or weakness
32. unexpected muscle pain
33. frequent infections
These symptoms may be the first signs of a serious reaction. A healthcare provider should examine you to decide if you should continue taking NEURONTIN.
4. Serious breathing problems. Serious breathing problems can happen when NEURONTIN is taken with other medicines (such as opioid pain medicines) that can cause severe sleepiness or decreased awareness, or when it is taken by someone who already has breathing problems. Call your healthcare provider or get medical help right away if you have any of the following symptoms:

- feel short of breath
- breathing slower than normal

- feel very tired
- confusion

- dizziness
- headache

Be sure that your caregiver or family members know which symptoms may be serious so they can call your healthcare provider or get medical help if you are unable to seek treatment on your own.

Your healthcare provider may lower your dose or stop your treatment with NEURONTIN if you have serious breathing problems.

What is NEURONTIN?

NEURONTIN is a prescription medicine used to treat:

- pain from damaged nerves (postherpetic pain) that follows healing of shingles (a painful rash that comes after a herpes zoster infection) in adults.
- partial seizures when taken together with other medicines in adults and children 3 years of age and older with seizures.

It is not known if NEURONTIN is safe and effective to treat:

- children with pain from damaged nerves from a painful rash caused by the chicken pox virus.
- partial seizures in children under 3 years of age.

Do not take NEURONTIN if you:

- are allergic to gabapentin or any of the other ingredients in NEURONTIN. See the end of this Medication Guide for a complete list of ingredients in NEURONTIN.

Before taking NEURONTIN, tell your healthcare provider about all of your medical conditions including if you:

- have or have had kidney problems or are on hemodialysis.
- have or have had depression, mood problems, or suicidal thoughts or behavior.
- have a history of drug abuse.
- have diabetes.
- have breathing problems.
- are pregnant or plan to become pregnant. It is not known if NEURONTIN can harm your unborn baby. Tell your healthcare provider right away if you become pregnant while taking NEURONTIN. You and your healthcare provider will decide if you should take NEURONTIN while you are pregnant.
  - Pregnancy Registry: If you become pregnant while taking NEURONTIN, talk to your healthcare provider about registering with the North American Antiepileptic Drug (NAAED) Pregnancy Registry. The purpose of this registry is to collect information about the safety of antiepileptic drugs during pregnancy. You can enroll in this registry by calling 1-888-233-2334 or visiting http://www.aedpregnancyregistry.org/.
- are breastfeeding or plan to breastfeed. NEURONTIN can pass into breast milk. You and your healthcare provider should decide how you will feed your baby while you take NEURONTIN.

Tell your healthcare provider about all the medicines you take, including prescription and over-the-counter medicines, vitamins, and herbal supplements.

Especially tell your healthcare provider if you take:

- any opioid pain medicine such as morphine, hydrocodone, oxycodone, or buprenorphine.
- any medicines for anxiety (such as lorazepam) or insomnia (such as zolpidem), or any medicines that make you sleepy. You may have a higher chance for dizziness, sleepiness, or breathing problems if these medicines are taken with NEURONTIN.

Taking NEURONTIN with certain other medicines can cause side effects or affect how well they work. Do not start or stop other medicines without talking to your healthcare provider.

Know the medicines you take. Keep a list of them and show it to your healthcare provider and pharmacist when you get a new medicine.

How should I take NEURONTIN?

- Take NEURONTIN exactly as prescribed. Your healthcare provider will tell you how much NEURONTIN to take.
- Do not change your dose of NEURONTIN without talking to your healthcare provider.
- Do not stop taking NEURONTIN without talking to your healthcare provider first. If you stop taking NEURONTIN suddenly, you may develop side effects.
- NEURONTIN can be taken with or without food.
- Swallow NEURONTIN capsules whole with water.
- If you take NEURONTIN tablets and break a tablet in half, the unused half of the tablet should be taken at your next scheduled dose. Half tablets not used within 28 days of breaking should be thrown away.
- If you take an antacid containing aluminum and magnesium, such as Maalox, Mylanta, Gelusil, Gaviscon, or Di-Gel, you should wait at least 2 hours before taking your next dose of NEURONTIN.
- In case of overdose, get medical help or contact a live Poison Center expert right away at 1-800-222-1222. Advice is also available online at poisonhelp.org.

What should I avoid while taking NEURONTIN?

- Do not drink alcohol or take other medicines that make you sleepy or dizzy while taking NEURONTIN without first talking with your healthcare provider. Taking NEURONTIN with alcohol or drugs that cause sleepiness or dizziness may make your sleepiness or dizziness worse.
- Do not drive, operate heavy machinery, or do other dangerous activities until you know how NEURONTIN affects you. NEURONTIN can slow your thinking and motor skills.

What are the possible side effects of NEURONTIN?

NEURONTIN may cause serious side effects, including:

- See “What is the most important information I should know about NEURONTIN?”
- problems driving while using NEURONTIN. See “What should I avoid while taking NEURONTIN?”
- sleepiness and dizziness, which could increase your chance of having an accidental injury, including falls.

The most common side effects of NEURONTIN include:

- lack of coordination
- viral infection
- difficulty with speaking
- tremor
- swelling, usually of legs and feet
- feeling tired
- fever

- feeling drowsy
- nausea and vomiting
- jerky movements
- difficulty with coordination
- double vision
- unusual eye movement

Tell your healthcare provider if you have any side effect that bothers you or that does not go away.

These are not all the possible side effects of NEURONTIN. For more information, ask your healthcare provider or pharmacist.

Call your doctor for medical advice about side effects. You may report side effects to FDA at 1-800-FDA-1088.

How should I store NEURONTIN?

- Store NEURONTIN capsules and tablets at room temperature between 68°F to 77°F (20°C to 25°C).
- Store NEURONTIN oral solution in the refrigerator between 36°F to 46°F (2°C to 8°C).

Keep NEURONTIN and all medicines out of the reach of children.

General information about the safe and effective use of NEURONTIN.

Medicines are sometimes prescribed for purposes other than those listed in a Medication Guide. Do not use NEURONTIN for a condition for which it was not prescribed. Do not give NEURONTIN to other people, even if they have the same symptoms that you have. It may harm them. You can ask your pharmacist or healthcare provider for information about NEURONTIN that is written for health professionals.

What are the ingredients in NEURONTIN?

Active ingredient: gabapentin.

Inactive ingredients in the capsules: cornstarch, FD&C Blue No. 2, gelatin, lactose, talc, and titanium dioxide.

The 300-mg capsule shell also contains: yellow iron oxide.

The 400-mg capsule shell also contains: red iron oxide and yellow iron oxide.

Inactive ingredients in the tablets: candelilla wax, copovidone, cornstarch, hydroxypropyl cellulose, magnesium stearate, poloxamer 407, and talc.

Inactive ingredients in the oral solution: artificial cool strawberry anise flavor, glycerin, purified water, and xylitol.

Distributed by:
Viatris Specialty LLC
Morgantown, WV 26505 U.S.A.
© 2025 Viatris Inc.

NEURONTIN is a registered trademark of UPJOHN US 1 LLC, a Viatris Company.
The brands listed are trademarks of their respective owners.
UPJ:MG:NRTNCTOS:R2

For more information, call Viatris at 1-877-446-3679 (1-877-4-INFO-RX).

This Medication Guide has been approved by the U.S. Food and Drug Administration Revised: 4/2025

PRINCIPAL DISPLAY PANEL – 100 mg

ALWAYS DISPENSE WITH MEDICATION GUIDE

NDC 58151-281-01

Neurontin®
(gabapentin) capsules

100 mg

100 Capsules Rx only

Store at 25°C (77°F); excursions
permitted between 15°C to 30°C
(59°F to 86°F) [see USP Controlled
Room Temperature].

Dispense in tight (USP),
child-resistant containers.

DOSAGE AND USE
See package insert for full
prescribing information.

Each capsule contains 100 mg
of gabapentin.

Distributed by:
Viatris Specialty LLC
Morgantown, WV 26505 U.S.A.

© 2024 Viatris Inc.

RUPJ281A

PRINCIPAL DISPLAY PANEL – 300 mg

ALWAYS DISPENSE WITH MEDICATION GUIDE

NDC 58151-282-01

Neurontin®
(gabapentin) capsules

300 mg

100 Capsules Rx only

Store at 25°C (77°F); excursions
permitted between 15°C to
30°C (59°F to 86°F) [see USP
Controlled Room Temperature].

Dispense in tight (USP),
child-resistant containers.

DOSAGE AND USE
See package insert for full
prescribing information.

Each capsule contains 300 mg
of gabapentin.

Distributed by:
Viatris Specialty LLC
Morgantown, WV 26505 U.S.A.

© 2024 Viatris Inc.

RUPJ282A

PRINCIPAL DISPLAY PANEL – 400 mg

ALWAYS DISPENSE WITH MEDICATION GUIDE

NDC 58151-283-01

Neurontin®
(gabapentin) capsules

400 mg

100 Capsules Rx only

Store at 25°C (77°F); excursions
permitted between 15°C to
30°C (59°F to 86°F) [see USP
Controlled Room Temperature].

Dispense in tight (USP),
child-resistant containers.

DOSAGE AND USE
See package insert for full
prescribing information.

Each capsule contains 400 mg
of gabapentin.

Distributed by:
Viatris Specialty LLC
Morgantown, WV 26505 U.S.A.

© 2024 Viatris Inc.

RUPJ283A

PRINCIPAL DISPLAY PANEL – 600 mg

ALWAYS DISPENSE WITH MEDICATION GUIDE

NDC 58151-284-01

Neurontin®
(gabapentin) tablets

600 mg

100 Tablets Rx only

Store at 25°C (77°F); excursions
permitted between 15°C to
30°C (59°F to 86°F) [see USP
Controlled Room Temperature].

Dispense in tight (USP),
child-resistant containers.

DOSAGE AND USE
See package insert for full
prescribing information.

Each tablet contains 600 mg
of gabapentin.

Distributed by:
Viatris Specialty LLC
Morgantown, WV 26505 U.S.A.

© 2024 Viatris Inc.

RUPJ284A

PRINCIPAL DISPLAY PANEL – 800 mg

ALWAYS DISPENSE WITH MEDICATION GUIDE

NDC 58151-285-01

Neurontin®
(gabapentin) tablets

800 mg

100 Tablets Rx only

Store at 25°C (77°F); excursions
permitted between 15°C to
30°C (59°F to 86°F) [see USP
Controlled Room Temperature].

Dispense in tight (USP),
child-resistant containers.

DOSAGE AND USE
See package insert for full
prescribing information.

Each tablet contains 800 mg
of gabapentin.

Distributed by:
Viatris Specialty LLC
Morgantown, WV 26505 U.S.A.

© 2024 Viatris Inc.

RUPJ286A

PRINCIPAL DISPLAY PANEL – Oral Solution, 250 mg/5 mL

ALWAYS DISPENSE WITH MEDICATION GUIDE

NDC 58151-290-35

Neurontin®
(gabapentin)
oral solution

250 mg per 5 mL

470 mL

Rx only

Store refrigerated,
2°C to 8°C (36°F to 46°F).

DOSAGE AND USE
See accompanying prescribing information.

Keep this and all drugs out of the reach
of children.

Each 5 mL of oral solution contains 250 mg
of gabapentin.

Distributed by:
Viatris Specialty LLC
Morgantown, WV 26505 U.S.A.

© 2024 Viatris Inc.

NEURONTIN is a registered trademark of
UPJOHN US 1 LLC, a Viatris Company.

UPJ:290:1C:R1